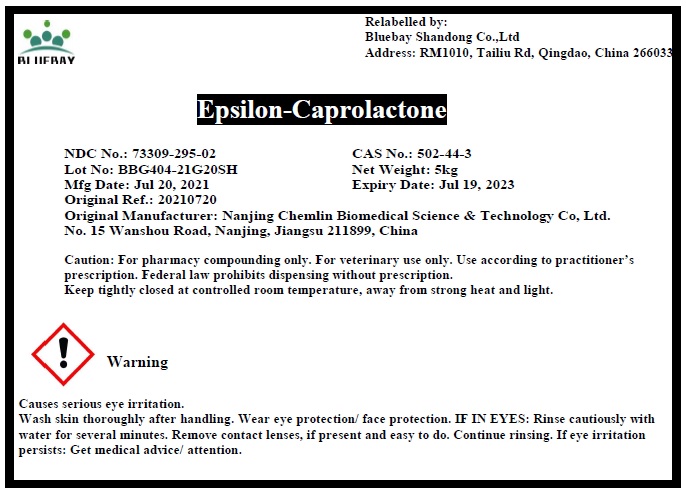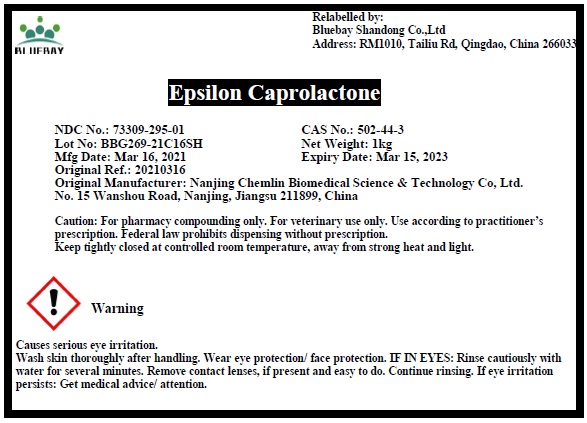 DRUG LABEL: Epsilon Caprolactone
NDC: 73309-295 | Form: LIQUID
Manufacturer: BLUEBAY SHANDONG CO.,LTD
Category: other | Type: BULK INGREDIENT
Date: 20210816

ACTIVE INGREDIENTS: CAPROLACTONE 1 kg/1 kg

Epsilon Caprolactone